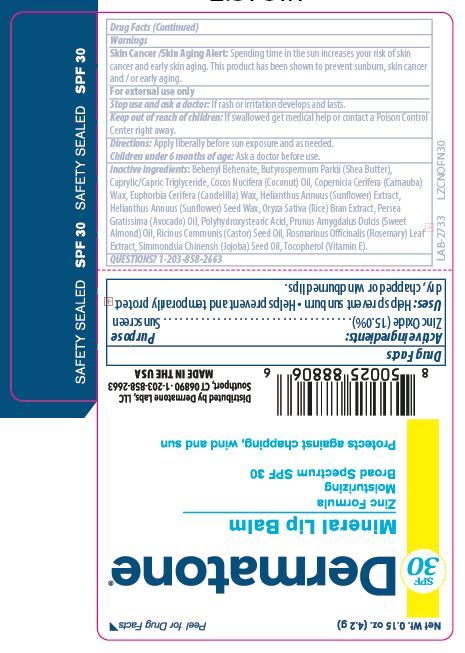 DRUG LABEL: SPF 30 - Zinc Oxide Lip Balm
NDC: 54414-107 | Form: STICK
Manufacturer: Dermatone
Category: otc | Type: HUMAN OTC DRUG LABEL
Date: 20251215

ACTIVE INGREDIENTS: ZINC OXIDE 150 mg/1 g
INACTIVE INGREDIENTS: COCONUT OIL 202 mg/1 g; WHITE WAX 182 mg/1 g; CASTOR OIL 162 mg/1 g

Drug Facts

Active ingredient

Zinc Oxide (15.0%)

Purpose

Sunscreen

Keep Out of Reach of Children

If swallowed get medical help or contact a Poison Control Center right away.

Uses

Prevents Sunburns

Warnings

Skin Cancer/Skin Aging Alert: Spending time in the sun increases your risk of skin cancer and early skin aging. This product has been shown to prevent sunburn, skin cancer and/or early aging.

For external use only: Stop use and ask a doctor: if rash or irritation develops and lasts.

Directions

Apply liberally 15 minutes before sun exposure • reapply: after 80 minutes

of swimming or sweating • immediately after towel drying • at least every 2 hours • Sun

Protection Measures.Spending time in the sun increases your risk of skin cancer and

early skin aging • To decrease the risk, regularly use a sunscreen with a broad spectrum

SPF of 15 or higher and other sun protection measures including: limit time in the sun,

especially from 10 a.m. -2 p.m. • wear long-sleeve shirts, pants, hats and sunglasses. Children under 6 months: Ask a doctor.

Inactive Ingredients

Behenyl Behenate, Butyrospermum Parkii (Shea Butter), Caprylic/Capric Triglyceride, Cocos Nucifera (Coconut) Oil, Copernicia Cerifera (Carnauba) Wax, Euphorbia Cerifera (Candelilla) Wax, Helianthus Annuus (Sunflower) Extract, Helianthus Annuus (Sunflower) Seed Wax, Oryza Sativa (Rice) Bran Extract, Persea Gratissima (Avocado) Oil, Polyhydroxystearic Acid, Prunus Amygdalus Dulcis (Sweet Almond) Oil, Ricinus Communis (Castor) Seed Oil, Rosmarinus Officinalis (Rosemary) Leaf Extract, Simmondsia Chinensis (Jojoba) Seed Oil, Tocopherol (Vitamin E).